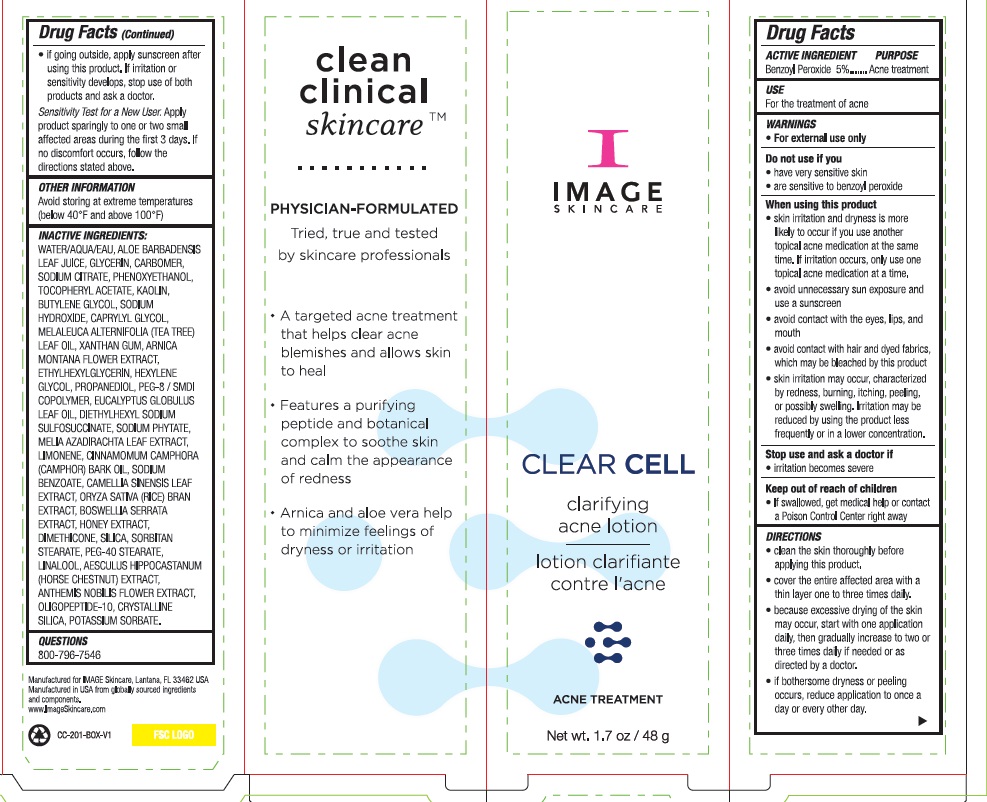 DRUG LABEL: Clear Cell Clarifying Acne
NDC: 62742-4208 | Form: LOTION
Manufacturer: Allure Labs
Category: otc | Type: HUMAN OTC DRUG LABEL
Date: 20241209

ACTIVE INGREDIENTS: BENZOYL PEROXIDE 50 mg/1 g
INACTIVE INGREDIENTS: SODIUM CITRATE; CAPRYLYL GLYCOL; HONEY; WATER; ALOE VERA LEAF; HEXYLENE GLYCOL; PHYTATE SODIUM; CAMPHOR OIL; GREEN TEA LEAF; ARNICA MONTANA FLOWER; SORBITAN MONOSTEARATE; GLYCERIN; .ALPHA.-TOCOPHEROL ACETATE; KAOLIN; BUTYLENE GLYCOL; TEA TREE OIL; XANTHAN GUM; ETHYLHEXYLGLYCERIN; PROPANEDIOL; PEG-8/SMDI COPOLYMER; DOCUSATE SODIUM; AZADIRACHTA INDICA LEAF; LIMONENE, (+)-; SODIUM BENZOATE; RICE BRAN; HORSE CHESTNUT; POTASSIUM SORBATE; PEG-40 STEARATE; INDIAN FRANKINCENSE; DIMETHICONE; CHAMAEMELUM NOBILE FLOWER; SODIUM HYDROXIDE; EUCALYPTUS OIL; PHENOXYETHANOL; SILICON DIOXIDE; LINALOOL, (+/-)-; OLIGOPEPTIDE-10; CARBOMER HOMOPOLYMER, UNSPECIFIED TYPE

Drug Facts

Active Ingredient

Benzoyl Peroxide 5 %

Purpose:

Acne Treatment

Use:

For the treatment of acne

Warning

For external use only

Do not use if you

have very sensitive skin

are sensitive to benzoyl peroxide

When using this product

Skin irritaion and dryness is more likely to occur if you use another topical acne medication at the same time. If irritation occurs,only use one topical acne medication at a time

Avoid unnecessary sun exposure and use a sunscreen

Aviod contact with the eyes, lips, and mouth

Avoid contact with hair and dyed fabrics,which may be bleached by this product

Skin irritation may occur,characterized by redness, burning, itching, peeling, or possibly swelling. Irritation may be reduced by using the product less frequently or in a lower concentration

Stop use and ask a doctor if

Irritation becomes severe

Keep out of reach of children

If swallowed, get medical help or contact a poison control center right away

DOSAGE AND ADMINISTRATION

Direction

Clean the skin thoroughly before applying this product

Cover the entire affected area with a thin layer one to three time daily

Because excessive drying of the skin may occur, start with one application daily, then gradually increase to two or three times daily if needed or as directed by a doctor

If bothersome dryness or peeling occurs, reduce application to once a day or every other day

Other information

Avoid storing at extreme temperatures (below 40°F and above 100°F)

Inactive ingredients

Water/Aqua/Eau,Aloe Barbadensis

Leaf Juice,Glycerin,Carbomer,

Sodium Citrate, Phenoxyethanol,

Tocopheryl Acetate, Kaolin,

Butylene Glycol, Sodium

Hydroxide, Caprylyl Glycol,

Melaleuca Alternifolia (Tea Tree)

Leaf Oil, Xanthan Gum, Arnica

Montana Flower Extract,

Ethylhexylglycerin,Hexylene

Glycol, Propanediol, PEG-8/SMDI

Copolymer,Eucalyptus Globulus

Leaf Oil, Diethylhexyl Sodium

Sulfosuccinate, Sodium Phytate,

Melia Azadirachta Leaf Extract,

Limonene, Cinnamimum Camphora

(Camphor) Bark Oil, Sodium

Benzoate, Camellia Sinensis Leaf

Extract, Oryza Savita (Rice) Bran

Extract, Boswellia Serrata

Extract, Honey Extract,

Dimethicone, Silica, Sorbitan

Stearate, PEG-40 Stearate,

Linalool, Aesculus Hippocastanum

(Horse Chestnut) Extract,

Anthemis Nobilis Flower Extract,

Oligopeptide-10, Crystalline

Silica, Potassium Sorbate.